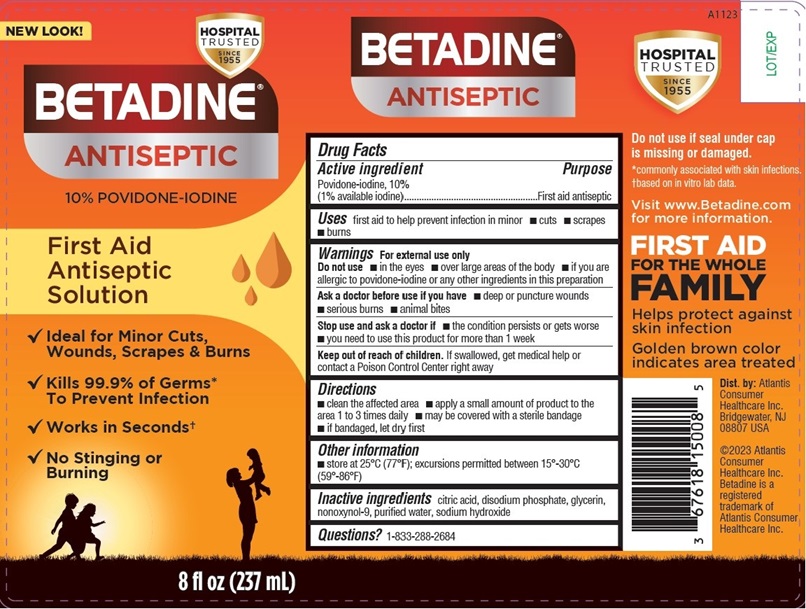 DRUG LABEL: Betadine
NDC: 67618-150 | Form: SOLUTION
Manufacturer: Atlantis Consumer Healthcare, Inc.
Category: otc | Type: HUMAN OTC DRUG LABEL
Date: 20260121

ACTIVE INGREDIENTS: POVIDONE-IODINE 10 mg/1 mL
INACTIVE INGREDIENTS: CITRIC ACID MONOHYDRATE; SODIUM PHOSPHATE, DIBASIC, MONOHYDRATE; GLYCERIN; NONOXYNOL-9; WATER; SODIUM HYDROXIDE

BETADINE® Solution
10% Povidone-iodine

Drug Facts

Active ingredient

Povidone-iodine, 10% (1% available iodine)

Purpose

First aid antiseptic

Uses

First aid to helpprevent infection in minor

- cuts
- scrapes
- burns

Do not use

- in the eyes
- over large areas of the body
- if you are allergic to povidone-iodine or any other ingredientsin this preparation

Ask a doctor before useif you have

- deep or puncture wounds
- serious burns
- animal bites

Stop use and ask a doctor if

- the condition persists or gets worse
- you need to use this product for more than 1 week

Keep out of reach of children.
If swallowed, getmedical help or contact a Poison Control Center right away

Directions

- clean the affected area
- apply a small amount of product to the area 1 to 3 timesdaily
- may be covered with a sterile bandage
- if bandaged, let dry first

Other information

- store at 25°C (77°F); excursions permitted between 15°-30°C(59°-86°F)

Inactive ingredients

citric acid, disodiumphosphate, glycerin, nonoxynol-9, purified water, sodium hydroxide

Dist.by:
Avrio Health L.P.
Stamford, CT 06901-3431

305541-0D

PACKAGE LABEL

BetadineSolution 8 fl oz Bottle
NDC: 67618-150-08